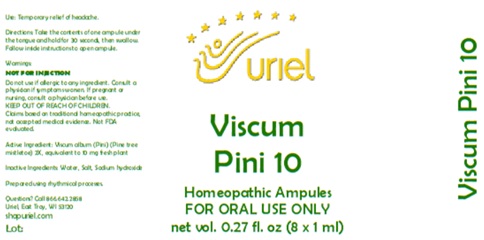 DRUG LABEL: Viscum Pini 10
NDC: 48951-9317 | Form: LIQUID
Manufacturer: Uriel Pharmacy Inc.
Category: homeopathic | Type: HUMAN OTC DRUG LABEL
Date: 20260225

ACTIVE INGREDIENTS: VISCUM ALBUM FRUITING TOP 2 [hp_X]/1 mL
INACTIVE INGREDIENTS: WATER; SODIUM CHLORIDE; SODIUM HYDROXIDE

Viscum Pini 10

PURPOSE

Use: Temporary relief of headache.

INDICATIONS AND USAGE

FOR ORAL USE ONLY

DOSAGE AND ADMINISTRATION

Directions: Take the contents of one ampule under the tongue and hold for 30 seconds, then swallow. Follow inside instructions to open ampule.

Warnings:
NOT FOR INJECTION
Do not use if allergic to any ingredient. Consult a physician if symptoms worsen. If pregnant or nursing, consult a physician before use.
Claims based on traditional homeopathic practice, not accepted medical evidence. Not FDA evaluated.

KEEP OUT OF REACH OF CHILDREN.

Active Ingredient: Viscum album - Pini (Pine tree mistletoe) 2X, equivalent to 10 mg fresh plant

Inactive Ingredients: Water, Salt, Sodium hydroxide

Prepared using rhythmical processes.

QUESTIONS

Questions? Call 866.642.2858 Uriel, East Troy, WI 53120 shopuriel.com Lot: